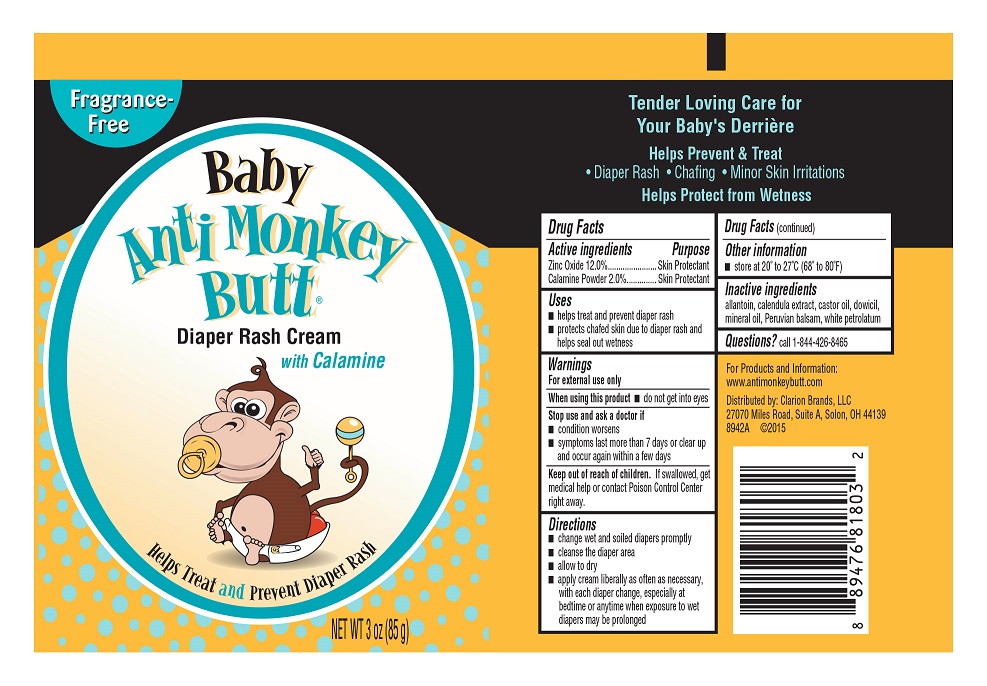 DRUG LABEL: BABY ANTI MONKEY BUTT DIAPER RASH
NDC: 69693-818 | Form: CREAM
Manufacturer: Clarion Brands, LLC
Category: otc | Type: HUMAN OTC DRUG LABEL
Date: 20251223

ACTIVE INGREDIENTS: ZINC OXIDE 0.12 g/1 g; FERRIC OXIDE RED 0.02 g/1 g
INACTIVE INGREDIENTS: ALLANTOIN; CALENDULA OFFICINALIS SEED OIL; CASTOR OIL; MINERAL OIL; BALSAM PERU; PETROLATUM; CALENDULA OFFICINALIS FLOWER; GLYCERIN; WATER

Drug Facts

Active Ingredients

Zinc Oxide 12.0%, Calamine Powder 2.0%

Purpose

Skin Protectant

Uses

- helps treat and prevent diaper rash
- protects chafed skin due to diaper rash and helps seal out wetness

Warnings

For external use only

When using this product

- do not get into eyes

Stop use and ask a doctor if

- condition worsens
- symptoms last more than 7 days or clear up and occur again within a few days

Keep out of reach of children

If swallowed, get medical help or contact Poison Control Center right away.

Directions

- change wet and soiled diapers promptly
- cleanse the diaper area
- allow to dry
- apply cream liberally as often as necessary, with each diaper change, especially at bedtime or anytime when exposure to wet diapers may be prolonged

Other information

- store at 20° to 27°C (68° to 80°F)

Inactive ingredients

allantoin, calendula extract, castor oil, dowicil, mineral oil, Peruvian balsam, white petrolatum

Questions?

Call 1-844-426-8465

PRINCIPAL DISPLAY PANEL

Fragrance-Free
Baby Anti Monkey Butt®
Diaper Rash Cream
with Calamine
Helps Treat and Prevent Diaper Rash
NET WT 3 oz (85 g)
Tender Loving Care for Your Baby's Derrière
Helps Prevent & Treat
• Diaper Rash • Chafing • Minor Skin Irritations
Helps Protect from Wetness
For Products and Information:
www.antimonkeybutt.com
Distributed by: Clarion Brands, LLC
27070 Miles Road, Suite A, Solon, OH 44139
8942A ©2015

Baby Anti Monkey Butt®
AML3000025C